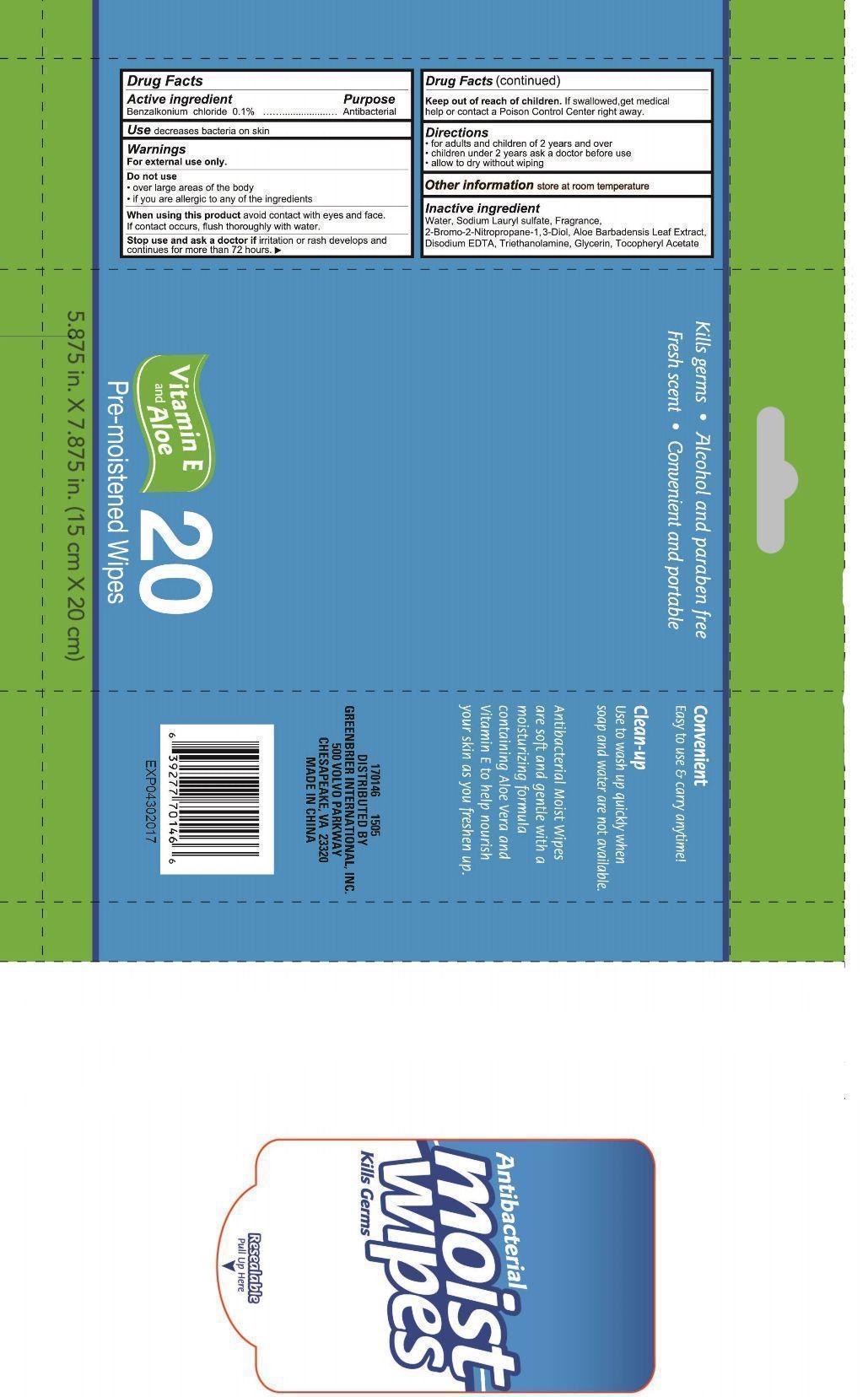 DRUG LABEL: Antibacterial Moist Wipes
NDC: 69733-558 | Form: swab
Manufacturer: JIANGSU TERRA MEDICAL TECHNOLOGY CO LTD
Category: otc | Type: HUMAN OTC DRUG LABEL
Date: 20150504

ACTIVE INGREDIENTS: BENZALKONIUM CHLORIDE 0.1 g/100 g
INACTIVE INGREDIENTS: WATER; SODIUM LAURYL SULFATE; 2-BROMO-2-NITROETHANOL; 2-METHYL-2-PROPYLPROPANE-1,3-DIOL; ALOE ARBORESCENS LEAF; DISODIUM EDTA-COPPER; TRIETHANOLAMINE BENZOATE; GLYCERIN; TOCOPHERYL RETINOATE

Active ingredient

Benzalkonium chloride 0.1%

Purpose

antibacterial

Use

decreases bacteria on skin

Warnings

for external use only

over large areas of the body

if you are allergic to ay of the ingredients

When using this product avoid contact with eyes and face.

if contact occurs,flush throughly with water

stop use and ask a doctor uf irritation or rash develops and continues for more than 72 hours.

Keep out of reach of children ,If swallowed ,get medical help or contact a Poison Control Center right away.

Directions

for adults and children of 2 years and over.

children under 2 years ask a doctor before use

allow to dry without wiping

INACTIVE INGREDIENT

water ,sodium lauryl sulfate,fragrance,2-bromo-2-nitropropane-1,3-diol,aloe barbadensis leaf extract,disodium EDTA,triethanolamine,glycerin,tocopheryl acetate.